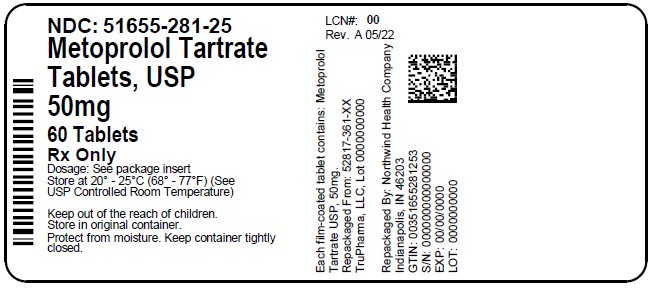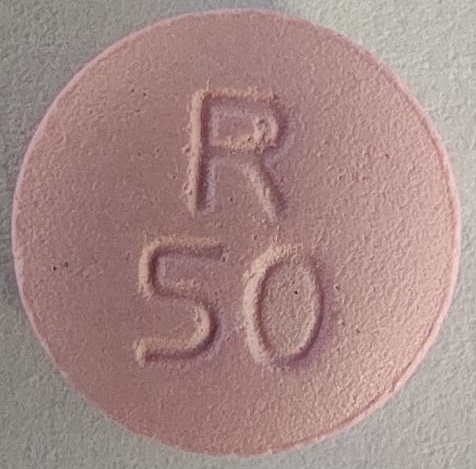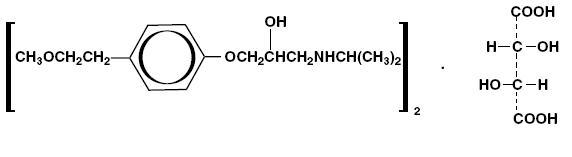 DRUG LABEL: Metoprolol Tartrate
NDC: 51655-281 | Form: TABLET, FILM COATED
Manufacturer: Northwind Health Company, LLC
Category: prescription | Type: HUMAN PRESCRIPTION DRUG LABEL
Date: 20260101

ACTIVE INGREDIENTS: METOPROLOL TARTRATE 50 mg/1 1
INACTIVE INGREDIENTS: LACTOSE MONOHYDRATE; SILICON DIOXIDE; HYPROMELLOSES; MAGNESIUM STEARATE; CELLULOSE, MICROCRYSTALLINE; POLYETHYLENE GLYCOL, UNSPECIFIED; TITANIUM DIOXIDE; TALC; D&C RED NO. 30; SODIUM STARCH GLYCOLATE TYPE A POTATO

METOPROLOL TARTRATE TABLETS, USP
TruPharma LLC
Rx only

DESCRIPTION

Metoprolol tartrate is a selective beta1-adrenoreceptor blocking agent, available as 25 mg, 37.5 mg, 50 mg, 75 mg and 100 mg tablets for oral administration. Metoprolol tartrate is (±)-1-(isopropylamino)-3-[ p-2-methoxyethyl)phenoxy]-2-propanol (2:1) dextro-tartrate salt. Its structural formula is:

Metoprolol tartrate, USP is a white, crystalline powder with a molecular weight of 684.82. It is very soluble in water; freely soluble in methylene chloride, in chloroform, and in alcohol; slightly soluble in acetone; and insoluble in ether.

Each tablet for oral administration contains 25 mg, 37.5 mg, 50 mg, 75 mg or 100 mg of metoprolol tartrate and the following inactive ingredients: lactose monohydrate, colloidal silicon dioxide, hypromellose, magnesium stearate, microcrystalline cellulose, polyethylene glycol, titanium dioxide, sodium starch glycolate, talc and D & C Red #30 Aluminium Lake.

CLINICAL PHARMACOLOGY

Mechanism of Action

Metoprolol is a beta1-selective (cardioselective) adrenergic receptor blocker. This preferential effect is not absolute, however, and at higher plasma concentrations, metoprolol also inhibits beta2 adrenoreceptors, chiefly located in the bronchial and vascular musculature.

Clinical pharmacology studies have demonstrated the beta-blocking activity of metoprolol, as shown by (1) reduction in heart rate and cardiac output at rest and upon exercise, (2) reduction of systolic blood pressure upon exercise, (3) inhibition of isoproterenol-induced tachycardia, and (4) reduction of reflex orthostatic tachycardia.
Hypertension

The mechanism of the antihypertensive effects of beta-blocking agents has not been fully elucidated. However, several possible mechanisms have been proposed: (1) competitive antagonism of catecholamines at peripheral (especially cardiac) adrenergic neuron sites, leading to decreased cardiac output; (2) a central effect leading to reduced sympathetic outflow to the periphery; and (3) suppression of renin activity.
Angina Pectoris

By blocking catecholamine-induced increases in heart rate, in velocity and extent of myocardial contraction, and in blood pressure, metoprolol reduces the oxygen requirements of the heart at any given level of effort, thus making it useful in the long-term management of angina pectoris.
Myocardial Infarction

The precise mechanism of action of metoprolol in patients with suspected or definite myocardial infarction is not known.

Pharmacodynamics

Relative beta1 selectivity is demonstrated by the following: (1) In healthy subjects, metoprolol is unable to reverse the beta2-mediated vasodilating effects of epinephrine. This contrasts with the effect of nonselective (beta1 plus beta2) beta-blockers, which completely reverse the vasodilating effects of epinephrine. (2) In asthmatic patients, metoprolol reduces FEV1 and FVC significantly less than a nonselective beta-blocker, propranolol, at equivalent beta1-receptor blocking doses.

Metoprolol has no intrinsic sympathomimetic activity, and membrane-stabilizing activity is detectable only at doses much greater than required for beta-blockade. Animal and human experiments indicate that metoprolol slows the sinus rate and decreases AV nodal conduction.

Significant beta-blocking effect (as measured by reduction of exercise heart rate) occurs within one hour after oral administration, and its duration is dose related. For example, a 50% reduction of the maximum effect after single oral doses of 20 mg, 50 mg, and 100 mg occurred at 3.3 hours, 5 hours and 6.4 hours, respectively, in normal subjects. After repeated oral dosages of 100 mg twice daily, a significant reduction in exercise systolic blood pressure was evident at 12 hours. When the drug was infused over a 10 minute period, in normal volunteers, maximum beta-blockade was achieved at approximately 20 minutes. Equivalent maximal beta-blocking effect is achieved with oral and intravenous doses in the ratio of approximately 2.5:1.

There is a linear relationship between the log of plasma levels and reduction of exercise heart rate. However, antihypertensive activity does not appear to be related to plasma levels. Because of variable plasma levels attained with a given dose and lack of a consistent relationship of antihypertensive activity to dose, selection of proper dosage requires individual titration.

In several studies of patients with acute myocardial infarction, intravenous followed by oral administration of metoprolol caused a reduction in heart rate, systolic blood pressure and cardiac output. Stroke volume, diastolic blood pressure and pulmonary artery end diastolic pressure remained unchanged.

In patients with angina pectoris, plasma concentration measured at one hour is linearly related to the oral dose within the range of 50 mg to 400 mg. Exercise heart rate and systolic blood pressure are reduced in relation to the logarithm of the oral dose of metoprolol. The increase in exercise capacity and the reduction in left ventricular ischemia are also significantly related to the logarithm of the oral dose.

Pharmacokinetics

Absorption
The estimated oral bioavailability of immediate-release metoprolol is about 50% because of pre-systemic metabolism which is saturable leading to non-proportionate increase in the exposure with increased dose.

Distribution

Metoprolol is extensively distributed with a reported volume of distribution of 3.2 L/kg to 5.6 L/kg. About 10% of metoprolol in plasma is bound to serum albumin. Metoprolol is known to cross the placenta and is found in breast milk. Metoprolol is also known to cross the blood brain barrier following oral administration and CSF concentrations close to that observed in plasma have been reported. Metoprolol is not a significant P-glycoprotein substrate.

Metabolism

Metoprolol is primarily metabolized by CYP2D6. Metoprolol is a racemic mixture of R- and S- enantiomers, and when administered orally, it exhibits stereoselective metabolism that is dependent on oxidation phenotype. CYP2D6 is absent (poor metabolizers) in about 8% of Caucasians and about 2% of most other populations. Poor CYP2D6 metabolizers exhibit several-fold higher plasma concentrations of metoprolol than extensive metabolizers with normal CYP2D6 activity thereby decreasing metoprolol’s cardioselectivity.

Elimination

Elimination of metoprolol is mainly by biotransformation in the liver. The mean elimination half-life of metoprolol is 3 to 4 hours; in poor CYP2D6 metabolizers the half-life may be 7 to 9 hours. Approximately 95% of the dose can be recovered in urine. In most subjects (extensive metabolizers), less than 5% of an oral dose and less than 10% of an intravenous dose are excreted as unchanged drug in the urine. In poor metabolizers, up to 30% or 40% of oral or intravenous doses, respectively, may be excreted unchanged; the rest is excreted by the kidneys as metabolites that appear to have no beta-blocking activity. The renal clearance of the stereoisomers does not exhibit stereo-selectivity in renal excretion.

Special Populations

Geriatric Patients

The geriatric population may show slightly higher plasma concentrations of metoprolol as a combined result of a decreased metabolism of the drug in elderly population and a decreased hepatic blood flow. However, this increase is not clinically significant or therapeutically relevant.

Renal Impairment

The systemic availability and half-life of metoprolol in patients with renal failure do not differ to a clinically significant degree from those in normal subjects.

Hepatic Impairment

Since the drug is primarily eliminated by hepatic metabolism, hepatic impairment may impact the pharmacokinetics of metoprolol. The elimination half-life of metoprolol is considerably prolonged, depending on severity (up to 7.2 h).

Clinical Studies

Hypertension

In controlled clinical studies, metoprolol has been shown to be an effective antihypertensive agent when used alone or as concomitant therapy with thiazide-type diuretics, at dosages of 100 mg to 450 mg daily. In controlled, comparative, clinical studies, metoprolol has been shown to be as effective an antihypertensive agent as propranolol, methyldopa, and thiazide-type diuretics, to be equally effective in supine and standing positions.

Angina Pectoris

In controlled clinical trials, metoprolol, administered 2 or 4 times daily, has been shown to be an effective antianginal agent, reducing the number of angina attacks and increasing exercise tolerance. The dosage used in these studies ranged from 100 mg to 400 mg daily. A controlled, comparative, clinical trial showed that metoprolol was indistinguishable from propranolol in the treatment of angina pectoris.

Myocardial Infarction

In a large (1,395 patients randomized), double-blind, placebo-controlled clinical study, metoprolol was shown to reduce 3 month mortality by 36% in patients with suspected or definite myocardial infarction.

Patients were randomized and treated as soon as possible after their arrival in the hospital, once their clinical condition had stabilized and their hemodynamic status had been carefully evaluated. Subjects were ineligible if they had hypotension, bradycardia, peripheral signs of shock and/or more than minimal basal rales as signs of congestive heart failure. Initial treatment consisted of intravenous followed by oral administration of metoprolol or placebo, given in a coronary care or comparable unit. Oral maintenance therapy with metoprolol or placebo was then continued for 3 months. After this double-blind period, all patients were given metoprolol and followed up to one year.
The median delay from the onset of symptoms to the initiation of therapy was 8 hours in both the metoprolol and placebo treatment groups. Among patients treated with metoprolol, there were comparable reductions in 3 month mortality for those treated early (≤ 8 hours) and those in whom treatment was started later. Significant reductions in the incidence of ventricular fibrillation and in chest pain following initial intravenous therapy were also observed with metoprolol and were independent of the interval between onset of symptoms and initiation of therapy.

In this study, patients treated with metoprolol received the drug both very early (intravenously) and during a subsequent 3 month period, while placebo patients received no beta-blocker treatment for this period. The study thus was able to show a benefit from the overall metoprolol regimen but cannot separate the benefit of very early intravenous treatment from the benefit of later beta-blocker therapy. Nonetheless, because the overall regimen showed a clear beneficial effect on survival without evidence of an early adverse effect on survival, one acceptable dosage regimen is the precise regimen used in the trial. Because the specific benefit of very early treatment remains to be defined however, it is also reasonable to administer the drug orally to patients at a later time as is recommended for certain other beta-blockers.

INDICATIONS AND USAGE

Hypertension

Metoprolol tartrate tablets are indicated for the treatment of hypertension. They may be used alone or in combination with other antihypertensive agents.

Angina Pectoris

Metoprolol tartrate tablets are indicated in the long-term treatment of angina pectoris.

Myocardial Infarction

Metoprolol tartrate tablets are indicated in the treatment of hemodynamically stable patients with definite or suspected acute myocardial infarction to reduce cardiovascular mortality when used alone or in conjunction with intravenous metoprolol. Oral Metoprolol tartrate tablets therapy can be initiated after intravenous metoprolol therapy or, alternatively, oral treatment can begin within 3 to 10 days of the acute event. (See DOSAGE AND ADMINISTRATION, CONTRAINDICATIONS, and WARNINGS).

CONTRAINDICATIONS

Hypertension and Angina

Metoprolol tartrate tablets are contraindicated in sinus bradycardia, heart block greater than first degree, cardiogenic shock, and overt cardiac failure (see WARNINGS).

Hypersensitivity to metoprolol and related derivatives, or to any of the excipients; hypersensitivity to other beta-blockers (cross-sensitivity between beta-blockers can occur).
Sick-sinus syndrome.
Severe peripheral arterial circulatory disorders.

Myocardial Infarction

Metoprolol is contraindicated in patients with a heart rate < 45 beats/min; second- and third-degree heart block; significant first-degree heart block (P-R interval ≥ 0.24 sec); systolic blood pressure < 100 mmHg; or moderate to severe cardiac failure (see WARNINGS).

WARNINGS

Heart Failure

Beta-blockers, like metoprolol, can cause depression of myocardial contractility and may precipitate heart failure and cardiogenic shock. If signs or symptoms of heart failure develop, treat the patient according to recommended guidelines. It may be necessary to lower the dose of metoprolol or to discontinue it.

Ischemic Heart Disease

Do not abruptly discontinue metoprolol therapy in patients with coronary artery disease. Severe exacerbation of angina, myocardial infarction and ventricular arrhythmias have been reported in patients with coronary artery disease following the abrupt discontinuation of therapy with beta-blockers. When discontinuing chronically administered metoprolol, particularly in patients with coronary artery disease, the dosage should be gradually reduced over a period of 1 to 2 weeks and the patient should be carefully monitored. If angina markedly worsens or acute coronary insufficiency develops, metoprolol administration should be reinstated promptly, at least temporarily, and other measures appropriate for the management of unstable angina should be taken. Patients should be warned against interruption or discontinuation of therapy without the physician’s advice. Because coronary artery disease is common and may be unrecognized, it may be prudent not to discontinue metoprolol therapy abruptly even in patients treated only for hypertension.

Use During Major Surgery

Chronically administered beta-blocking therapy should not be routinely withdrawn prior to major surgery; however, the impaired ability of the heart to respond to reflex adrenergic stimuli may augment the risks of general anesthesia and surgical procedures.

Bradycardia

Bradycardia, including sinus pause, heart block, and cardiac arrest have occurred with the use of metoprolol. Patients with first-degree atrioventricular block, sinus node dysfunction or conduction disorders may be at increased risk. Monitor heart rate and rhythm in patients receiving metoprolol. If severe bradycardia develops, reduce or stop metoprolol.

Exacerbation of Bronchospastic Disease

Patients with bronchospastic disease, should, in general, not receive beta-blockers, including metoprolol. Because of its relative beta1 selectivity, however, metoprolol may be used in patients with bronchospastic disease who do not respond to, or cannot tolerate, other antihypertensive treatment. Because beta1 selectivity is not absolute use the lowest possible dose of metoprolol and consider administering metoprolol in smaller doses 3 times daily, instead of larger doses 2 times daily, to avoid the higher plasma levels associated with the longer dosing interval (see DOSAGE AND ADMINISTRATION). Bronchodilators, including beta2 agonists, should be readily available or administered concomitantly.

Diabetes and Hypoglycemia

Beta-blockers may mask tachycardia occurring with hypoglycemia, but other manifestations such as dizziness and sweating may not be significantly affected.

Pheochromocytoma

If metoprolol is used in the setting of pheochromocytoma, it should be given in combination with an alpha-blocker, and only after the alpha-blocker has been initiated. Administration of beta-blockers alone in the setting of pheochromocytoma has been associated with a paradoxical increase in blood pressure due to the attenuation of beta-mediated vasodilatation in skeletal muscle.

Thyrotoxicosis

Metoprolol may mask certain clinical signs (e.g., tachycardia) of hyperthyroidism. Avoid abrupt withdrawal of beta-blockade, which might precipitate a thyroid storm.

PRECAUTIONS

Risk of Anaphylactic Reactions

While taking beta-blockers, patients with a history of severe anaphylactic reaction to a variety of allergens may be more reactive to repeated challenge, either accidental, diagnostic or therapeutic. Such patients may be unresponsive to the usual doses of epinephrine used to treat allergic reaction.

Information for Patients

Advise patients to take metoprolol regularly and continuously, as directed, with or immediately following meals. If a dose should be missed, the patient should take only the next scheduled dose (without doubling it). Patients should not discontinue metoprolol without consulting the physician.

Advise patients (1) to avoid operating automobiles and machinery or engaging in other tasks requiring alertness until the patient’s response to therapy with metoprolol has been determined; (2) to contact the physician if any difficulty in breathing occurs; (3) to inform the physician or dentist before any type of surgery that he or she is taking metoprolol.

Drug Interactions

Catecholamine-Depleting Drugs

Catecholamine-depleting drugs (e.g., reserpine) may have an additive effect when given with beta-blocking agents or monoamine oxidase (MAO) inhibitors. Observe patients treated with metoprolol plus a catecholamine depletor for evidence of hypotension or marked bradycardia, which may produce vertigo, syncope, or postural hypotension. In addition, possibly significant hypertension may theoretically occur up to 14 days following discontinuation of the concomitant administration with an irreversible MAO inhibitor.

Digitalis Glycosides and Beta-Blockers

Both digitalis glycosides and beta-blockers slow atrioventricular conduction and decrease heart rate. Concomitant use can increase the risk of bradycardia. Monitor heart rate and PR interval.

Calcium Channel Blockers

Concomitant administration of a beta-adrenergic antagonist with a calcium channel blocker may produce an additive reduction in myocardial contractility because of negative chronotropic and inotropic effects.

CYP2D6 Inhibitors

Potent inhibitors of the CYP2D6 enzyme may increase the plasma concentration of metoprolol which would mimic the pharmacokinetics of CYP2D6 poor metabolizer (see CLINICAL PHARMACOLOGY: Pharmacokinetics). Increase in plasma concentrations of metoprolol would decrease the cardioselectivity of metoprolol. Known clinically significant potent inhibitors of CYP2D6 are antidepressants such as fluvoxamine, fluoxetine, paroxetine, sertraline, bupropion, clomipramine and desipramine; antipsychotics such as chlorpromazine, fluphenazine, haloperidol and thioridazine; antiarrhythmics such as quinidine or propafenone; antiretrovirals such as ritonavir; antihistamines such as diphenhydramine; antimalarials such as hydroxychloroquine or quinidine; antifungals such as terbinafine.

Hydralazine

Concomitant administration of hydralazine may inhibit presystemic metabolism of metoprolol leading to increased concentrations of metoprolol.

Alpha-Adrenergic Agents

Antihypertensive effect of alpha-adrenergic blockers such as guanethidine, betanidine, reserpine, alpha-methyldopa or clonidine may be potentiated by beta-blockers including metoprolol. Beta- adrenergic blockers may also potentiate the postural hypotensive effect of the first dose of prazosin, probably by preventing reflex tachycardia. On the contrary, beta-adrenergic blockers may also potentiate the hypertensive response to withdrawal of clonidine in patients receiving concomitant clonidine and beta-adrenergic blocker. If a patient is treated with clonidine and metoprolol concurrently, and clonidine treatment is to be discontinued, stop metoprolol several days before clonidine is withdrawn. Rebound hypertension that can follow withdrawal of clonidine may be increased in patients receiving concurrent beta-blocker treatment.

Ergot Alkaloid

Concomitant administration with beta-blockers may enhance the vasoconstrictive action of ergot alkaloids.

Dipyridamole

In general, administration of a beta-blocker should be withheld before dipyridamole testing, with careful monitoring of heart rate following the dipyridamole injection.

Carcinogenesis, Mutagenesis, Impairment of Fertility

Long-term studies in animals have been conducted to evaluate carcinogenic potential. In a 2-year study in rats at three oral dosage levels of up to 800 mg/kg per day, there was no increase in the development of spontaneously occurring benign or malignant neoplasms of any type. The only histologic changes that appeared to be drug-related were an increased incidence of generally mild focal accumulation of foamy macrophages in pulmonary alveoli and a slight increase in biliary hyperplasia. In a 21-month study in Swiss albino mice at three oral dosage levels of up to 750 mg/kg per day, benign lung tumors (small adenomas) occurred more frequently in female mice receiving the highest dose than in untreated control animals. There was no increase in malignant or total (benign plus malignant) lung tumors, or in the overall incidence of tumors or malignant tumors. This 21-month study was repeated in CD-1 mice, and no statistically or biologically significant differences were observed between treated and control mice of either sex for any type of tumor.

All mutagenicity tests performed (a dominant lethal study in mice, chromosome studies in somatic cells, a Salmonella/mammalian-microsome mutagenicity test, and a nucleus anomaly test in somatic interphase nuclei) were negative.

Reproduction toxicity studies in mice, rats and rabbits did not indicate teratogenic potential for metoprolol tartrate. Embryotoxicity and/or fetotoxicity in rats and rabbits were noted starting at doses of 50 mg/kg in rats and 25 mg/kg in rabbits, as demonstrated by increases in preimplantation loss, decreases in the number of viable fetuses per dose, and/or decreases in neonatal survival. High doses were associated with some maternal toxicity, and growth delay of the offspring in utero, which was reflected in minimally lower weights at birth. The oral NOAELs for embryo-fetal development in mice, rats, and rabbits were considered to be 25, 200, and 12.5 mg/kg. This corresponds to dose levels that are approximately 0.3 times, 4 times, and 0.5 times, respectively, when based on surface area, the maximum human oral dose (8 mg/kg/day) of metoprolol tartrate. Metoprolol tartrate has been associated with reversible adverse effects on spermatogenesis starting at oral dose levels of 3.5 mg/kg in rats (a dose that is only 0.1 times the human dose, when based on surface area), although other studies have shown no effect of metoprolol tartrate on reproductive performance in male rats.

Pregnancy

Pregnancy Category C

Upon confirming the diagnosis of pregnancy, women should immediately inform their doctor. Metoprolol has been shown to increase postimplantation loss and decrease neonatal survival in rats at doses up to 11 times the maximum daily human dose of 450 mg, when based on surface area. Distribution studies in mice confirm exposure of the fetus when metoprolol is administered to the pregnant animal. These limited animal studies do not indicate direct or indirect harmful effects with respect to teratogenicity (see PRECAUTIONS: Carcinogenesis, Mutagenesis, Impairment of Fertility).

There are no adequate and well controlled studies in pregnant women. The amount of data on the use of metoprolol in pregnant women is limited. The risk to the fetus/mother is unknown. Because animal reproduction studies are not always predictive of human response, this drug should be used during pregnancy only if clearly needed.

Nursing Mothers

Metoprolol is excreted in breast milk in a very small quantity. An infant consuming one liter of breast milk daily would receive a dose of less than 1 mg of the drug.

Fertility

The effects of metoprolol on the fertility of human have not been studied.
Metoprolol showed effects on spermatogenesis in male rats at a therapeutic dose level, but had no effect on rates of conception at higher doses in animal fertility studies (see PRECAUTIONS: Carcinogenesis, Mutagenesis, Impairment of Fertility).

Pediatric Use

Safety and effectiveness in pediatric patients have not been established.

Geriatric Use

Clinical trials of metoprolol in hypertension did not include sufficient numbers of elderly patients to determine whether patients over 65 years of age differ from younger subjects in their response to metoprolol. Other reported clinical experience in elderly hypertensive patients has not identified any difference in response from younger patients.
In worldwide clinical trials of metoprolol in myocardial infarction, where approximately 478 patients were over 65 years of age (0 over 75 years of age), no age related differences in safety and effectiveness were found. Other reported clinical experience in myocardial infarction has not identified differences in response between the elderly and younger patients. However, greater sensitivity of some elderly individuals taking metoprolol cannot be categorically ruled out. Therefore, in general, it is recommended that dosing proceed with caution in this population.

ADVERSE REACTIONS

Hypertension and Angina

Most adverse effects have been mild and transient.

Central Nervous System

Tiredness and dizziness have occurred in about 10 of 100 patients. Depression has been reported in about 5 of 100 patients. Mental confusion and short-term memory loss have been reported. Headache, nightmares, and insomnia have also been reported.

Cardiovascular

Shortness of breath and bradycardia have occurred in approximately 3 of 100 patients. Cold extremities; arterial insufficiency, usually of the Raynaud type; palpitations; congestive heart failure; peripheral edema; and hypotension have been reported in about 1 of 100 patients. Gangrene in patients with preexisting severe peripheral circulatory disorders has also been reported very rarely (see CONTRAINDICATIONS, WARNINGS, and PRECAUTIONS).

Respiratory

Wheezing (bronchospasm) and dyspnea have been reported in about 1 of 100 patients (see WARNINGS). Rhinitis has also been reported.

Gastrointestinal

Diarrhea has occurred in about 5 of 100 patients. Nausea, dry mouth, gastric pain, constipation, flatulence, and heartburn have been reported in about 1 of 100 patients. Vomiting was a common occurrence. Post-marketing experience reveals very rare reports of hepatitis, jaundice and nonspecific hepatic dysfunction. Isolated cases of transaminase, alkaline phosphatase, and lactic dehydrogenase elevations have also been reported.

Hypersensitive Reactions

Pruritus or rash have occurred in about 5 of 100 patients. Very rarely, photosensitivity and worsening of psoriasis has been reported.

Miscellaneous

Peyronie’s disease has been reported in fewer than 1 of 100,000 patients. Musculoskeletal pain, blurred vision, and tinnitus have also been reported.

There have been rare reports of reversible alopecia, agranulocytosis, and dry eyes. Discontinuation of the drug should be considered if any such reaction is not otherwise explicable. There have been very rare reports of weight gain, arthritis, and retroperitoneal fibrosis (relationship to metoprolol has not been definitely established).

The oculomucocutaneous syndrome associated with the beta-blocker practolol has not been reported with metoprolol.

Myocardial Infarction

Central Nervous System

Tiredness has been reported in about 1 of 100 patients. Vertigo, sleep disturbances, hallucinations, headache, dizziness, visual disturbances, confusion, and reduced libido have also been reported, but a drug relationship is not clear.

Cardiovascular

In the randomized comparison of metoprolol and placebo described in the CLINICAL PHARMACOLOGYsection, the following adverse reactions were reported:

 | Metoprolol Tartrate Tablets | Placebo
Hypotension (systolic BP < 90 mm Hg) | 27.4% | 23.2%
Bradycardia (heart rate < 40 beats/min) | 15.9% | 6.7%
Second- or third-degree heart block | 4.7% | 4.7%
First-degree heart block (P-R ≥ 0.26 sec) | 5.3% | 1.9%
Heart failure | 27.5% | 29.6%

Respiratory

Dyspnea of pulmonary origin has been reported in fewer than 1 of 100 patients.

Gastrointestinal

Nausea and abdominal pain have been reported in fewer than 1 of 100 patients.

Dermatologic

Rash and worsened psoriasis have been reported, but a drug relationship is not clear.

Miscellaneous

Unstable diabetes and claudication have been reported, but a drug relationship is not clear.

Potential Adverse Reactions

A variety of adverse reactions not listed above have been reported with other beta-adrenergic blocking agents and should be considered potential adverse reactions to metoprolol.

Central Nervous System

Reversible mental depression progressing to catatonia; an acute reversible syndrome characterized by disorientation for time and place, short-term memory loss, emotional lability, slightly clouded sensorium, and decreased performance on neuropsychometrics.

Cardiovascular

Intensification of AV block (see CONTRAINDICATIONS).

Hematologic

Agranulocytosis, nonthrombocytopenic purpura and thrombocytopenic purpura.

Hypersensitive Reactions

Fever combined with aching and sore throat, laryngospasm and respiratory distress.

Post-Marketing Experience

The following adverse reactions have been reported during post-approval use of metoprolol: confusional state, an increase in blood triglycerides and a decrease in High Density Lipoprotein (HDL). Because these reports are from a population of uncertain size and are subject to confounding factors, it is not possible to reliably estimate their frequency.

OVERDOSAGE

Acute Toxicity

Several cases of overdosage have been reported, some leading to death.
Oral LD50's (mg/kg): mice, 1,158 to 2,460; rats, 3,090 to 4,670.

Signs and Symptoms

Potential signs and symptoms associated with overdosage with metoprolol are bradycardia, hypotension, bronchospasm, myocardial infarction, cardiac failure and death.

Management

There is no specific antidote.

In general, patients with acute or recent myocardial infarction may be more hemodynamically unstable than other patients and should be treated accordingly (see WARNINGS: Myocardial Infarction).

On the basis of the pharmacologic actions of metoprolol, the following general measures should be employed:

Elimination of the Drug

Gastric lavage should be performed.

Other clinical manifestations of overdose should be managed symptomatically based on modern methods of intensive care.

Hypotension

Administer a vasopressor, e.g., norepinephrine or dopamine.

Bronchospasm

Administer a beta2-stimulating agent and/or a theophylline derivative.

Cardiac Failure

Administer digitalis glycoside and diuretic. In shock resulting from inadequate cardiac contractility, consider administration of dobutamine, isoproterenol or glucagon.

DOSAGE AND ADMINISTRATION

Hypertension

Individualize the dosage of metoprolol tartrate tablets. Metoprolol tartrate tablets should be taken with or immediately following meals.

The usual initial dosage of metoprolol tartrate tablets is 100 mg daily in single or divided doses, whether used alone or added to a diuretic. Increase the dosage at weekly (or longer) intervals until optimum blood pressure reduction is achieved. In general, the maximum effect of any given dosage level will be apparent after one week of therapy. The effective dosage range of metoprolol tartrate tablets is 100 mg per day to 450 mg per day. Dosages above 450 mg per day have not been studied. While once daily dosing is effective and can maintain a reduction in blood pressure throughout the day, lower doses (especially 100 mg) may not maintain a full effect at the end of the 24-hour period, and larger or more frequent daily doses may be required. This can be evaluated by measuring blood pressure near the end of the dosing interval to determine whether satisfactory control is being maintained throughout the day. Beta1 selectivity diminishes as the dose of Metoprolol is increased.

Angina Pectoris

The dosage of metoprolol tartrate tablets should be individualized. Metoprolol tartrate tablets should be taken with or immediately following meals.
The usual initial dosage of metoprolol tartrate tablets is 100 mg daily, given in two divided doses. Gradually increase the dosage at weekly intervals until optimum clinical response has been obtained or there is pronounced slowing of the heart rate. The effective dosage range of metoprolol tartrate tablets is 100 mg per day to 450 mg per day. Dosages above 400 mg per day have not been studied. If treatment is to be discontinued, gradually decrease the dosage over a period of 1 to 2 weeks (see WARNINGS).

Myocardial Infarction

Early Treatment

During the early phase of definite or suspected acute myocardial infarction, initiate treatment with metoprolol tartrate tablets as soon as possible after the patient’s arrival in the hospital. Such treatment should be initiated in a coronary care or similar unit immediately after the patient’s hemodynamic condition has stabilized.

Begin treatment in this early phase with the intravenous administration of three bolus injections of 5 mg of metoprolol tartrate each; give the injections at approximately 2 minute intervals. During the intravenous administration of metoprolol, monitor blood pressure, heart rate, and electrocardiogram.

In patients who tolerate the full intravenous dose (15 mg), initiate metoprolol tartrate tablets, 50 mg every 6 hours, 15 minutes after the last intravenous dose and continue for 48 hours. Thereafter, the maintenance dosage is 100 mg twice daily (see Late Treatment below).

Start patients who appear not to tolerate the full intravenous dose on metoprolol tartrate tablets either 25 mg or 50 mg every 6 hours (depending on the degree of intolerance) 15 minutes after the last intravenous dose or as soon as their clinical condition allows. In patients with severe intolerance, discontinue metoprolol tartrate tablets (see WARNINGS).

Late Treatment

Start patients with contraindications to treatment during the early phase of suspected or definite myocardial infarction, patients who appear not to tolerate the full early treatment, and patients in whom the physician wishes to delay therapy for any other reason on metoprolol tartrate tablets, 100 mg twice daily, as soon as their clinical condition allows. Continue therapy for at least 3 months. Although the efficacy of metoprolol beyond 3 months has not been conclusively established, data from studies with other beta-blockers suggest that treatment should be continued for 1 to 3 years.

Special Populations

Pediatric Patients

No pediatric studies have been performed. The safety and efficacy of metoprolol in pediatric patients have not been established.

Renal Impairment

No dose adjustment of metoprolol tartrate tablets is required in patients with renal impairment.

Hepatic Impairment

Metoprolol blood levels are likely to increase substantially in patients with hepatic impairment. Therefore, metoprolol tartrate tablets should be initiated at low doses with cautious gradual dose titration according to clinical response.

Geriatric Patients (> 65 Years)

In general, use a low initial starting dose in elderly patients given their greater frequency of decreased hepatic, renal, or cardiac function, and of concomitant disease or other drug therapy.

Method of Administration

For oral treatment, the tablets should be swallowed unchewed with a glass of water. Metoprolol tartrate tablets should always be taken in standardized relation with meals. If the physician asks the patient to take metoprolol tartrate tablets either before breakfast or with breakfast, then the patient should continue taking metoprolol tartrate tablets with the same schedule during the course of therapy.

HOW SUPPLIED

Metoprolol Tartrate Tablets, USP are available containing 50 mg of metoprolol tartrate, USP.

The 50 mg tablets are film-coated, pink colored, round, biconvex tablets debossed with R 50 on one side and scored on the other side.

NDC 51655-281-25: Bottles of 60

Store at 20° to 25°C (68° to 77°F). [See USP Controlled Room Temperature.]

Protect from moisture.
Dispense in a tight, light-resistant container as defined in the USP using a child-resistant closure.

To report SUSPECTED ADVERSE REACTIONS, contact TruPharma, LLC at 1-813-444-6299 or FDA at 1-800-FDA-1088 or www.fda.gov/medwatch.

Distributed by:
TruPharma, LLC
Tampa, FL 33609

Manufactured by:
Rubicon Research Private Limited
Ambernath, Dist: Thane, 421506,
INDIA

Rev. 01,11/2018

PRINCIPAL DISPLAY PANEL

NDC: 51655-281-25